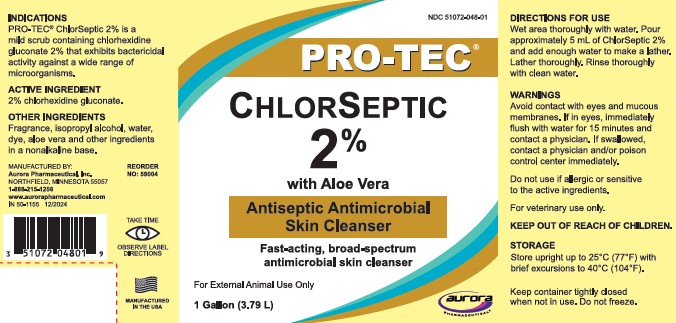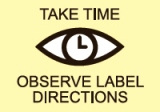 DRUG LABEL: Chlorhexidine Gluconate
NDC: 51072-048 | Form: SOLUTION
Manufacturer: Aurora Pharmaceutical, Inc.
Category: animal | Type: OTC ANIMAL DRUG LABEL
Date: 20250616

ACTIVE INGREDIENTS: CHLORHEXIDINE GLUCONATE 20 g/1 L

ChlorSeptic 2% with Aloe Vera

INDICATIONS

PRO-TEC® ChlorSeptic 2% is a mild scrub containing chlorhexidine gluconate 2% that exhibits bactericidal activity against a wide range of microorganisms.

ACTIVE INGREDIENT

2% chlorhexidine gluconate

DIRECTIONS FOR USE

Wet area thoroughly with water. Pour approximately 5 mL of ChlorSeptic 2% and add enough water to make a lather. Lather thoroughly. Rinse thoroughly with clean water.

WARNINGS

Avoid contact with eyes and mucous membranes. If in eyes, immediately flush with water for 15 minutes and contact a physician. If swallowed, contact a physician and/or poison control center immediately.

Do not use if allergic or sensitive to the active ingredients.

For veterinary use only.

KEEP OUT OF REACH OF CHILDREN.

STORAGE

Store upright up to 25°C (77°F) with brief excursionst to 40° C (104°F).

Keep container tightly closed when not in use. Do not freeze.

OTHER INGREDIENTS

Fragrance, isopropyl alcohol, water, dye, aloe vera and other ingredients in a nonalkaline base.

MANUFACTURED IN THE USA

REORDER NO: 59004

MANUFACTURED BY:
Aurora Pharmaceutical, Inc.
NORTHFIELD, MINNESOTA 55057
1-888-215-1256
www.aurorapharmaceutical.com

IN 50-1155 12/2024

PRINCIPAL DISPLAY PANEL - 1 Gallon Bottle Label

NDC 51072-048-01

PRO-TEC®

ChlorSeptic

2%

with Aloe Vera

Antiseptic Antimicrobial Skin Cleanser

Fast-acting, broad-spectrum antimicrobial skin cleanser

For External Animal Use Only

1 Gallon (3.79 L)

AURORA PHARMACEUTICAL®